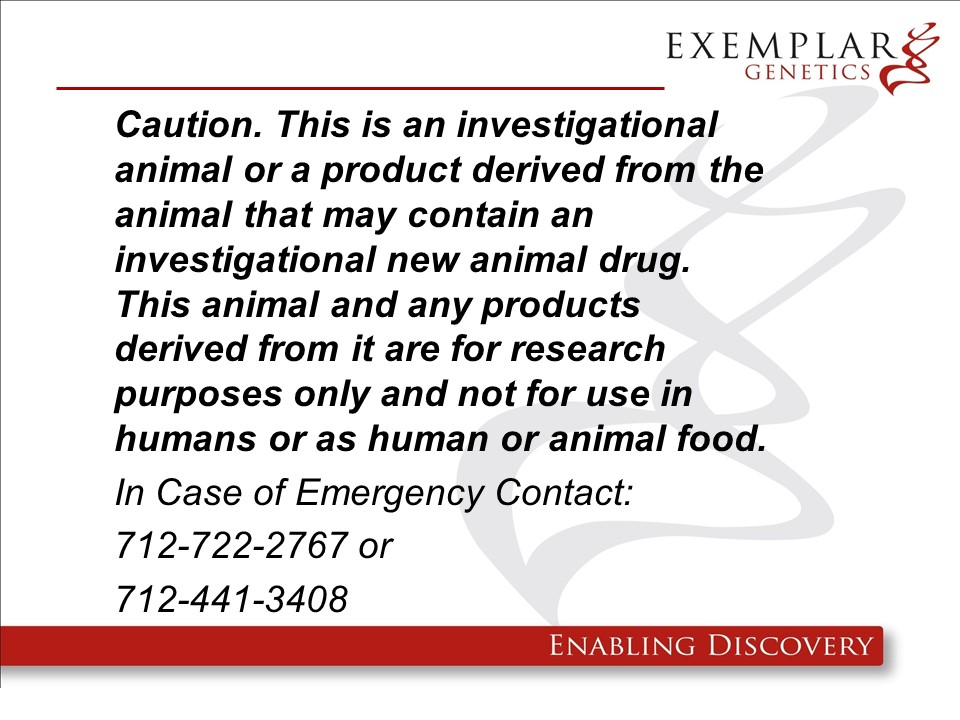 DRUG LABEL: ExeGen CLN2 miniswine
NDC: 86093-2004 | Form: NOT APPLICABLE
Manufacturer: Exemplar Genetics LLC (dba Precigen Exemplar)
Category: other | Type: INTENTIONAL ANIMAL GENOMIC ALTERATION LABEL
Date: 20250521

ACTIVE INGREDIENTS: CLN2 RDNA CONSTRUCT DISRUPTING EXON 6 OF CLN2 GENE IN YUCATAN MINIATURE SWINE 1 [arb'U]/1 [arb'U]

pCLN2 in miniswine

ExeGen CLN2 miniswine are genetically engineered yucatan miniature swine containing the rDNA construct pCLN2 which exhibit similar phenotypes to human patients with CLN2 disease. These pigs are intended to be used as large animal models of the human disease. We will not be requesting a food use authorization and the carcasses and all materials generated from these animals will be destroyed by incineration.

Product Definition: A specific line of Yucatan miniature pigs (Sus scrofa domesticus), including homozygous and heterozygous offspring resulting from a heterozygous founder, in which the CLN2 gene has been disrupted by the homologous recombination of a single copy of a mutated CLN2-PGK construct in exon 6 for use in biomedical research. The desirable animal will be a homozygote CLN2 R208X Blast Excised/R208X Blast Excised miniswine.

Warning: This product is from a genetically engineered animal and may contain an investigational new animal drug. It is for research purposes only and not for use in humans or as food/feed unless authorization has been granted by the US Food and Drug Administration. In case of emergency or release contact Exemplar Genetics at 712-722-2767 or 712-441-3408.